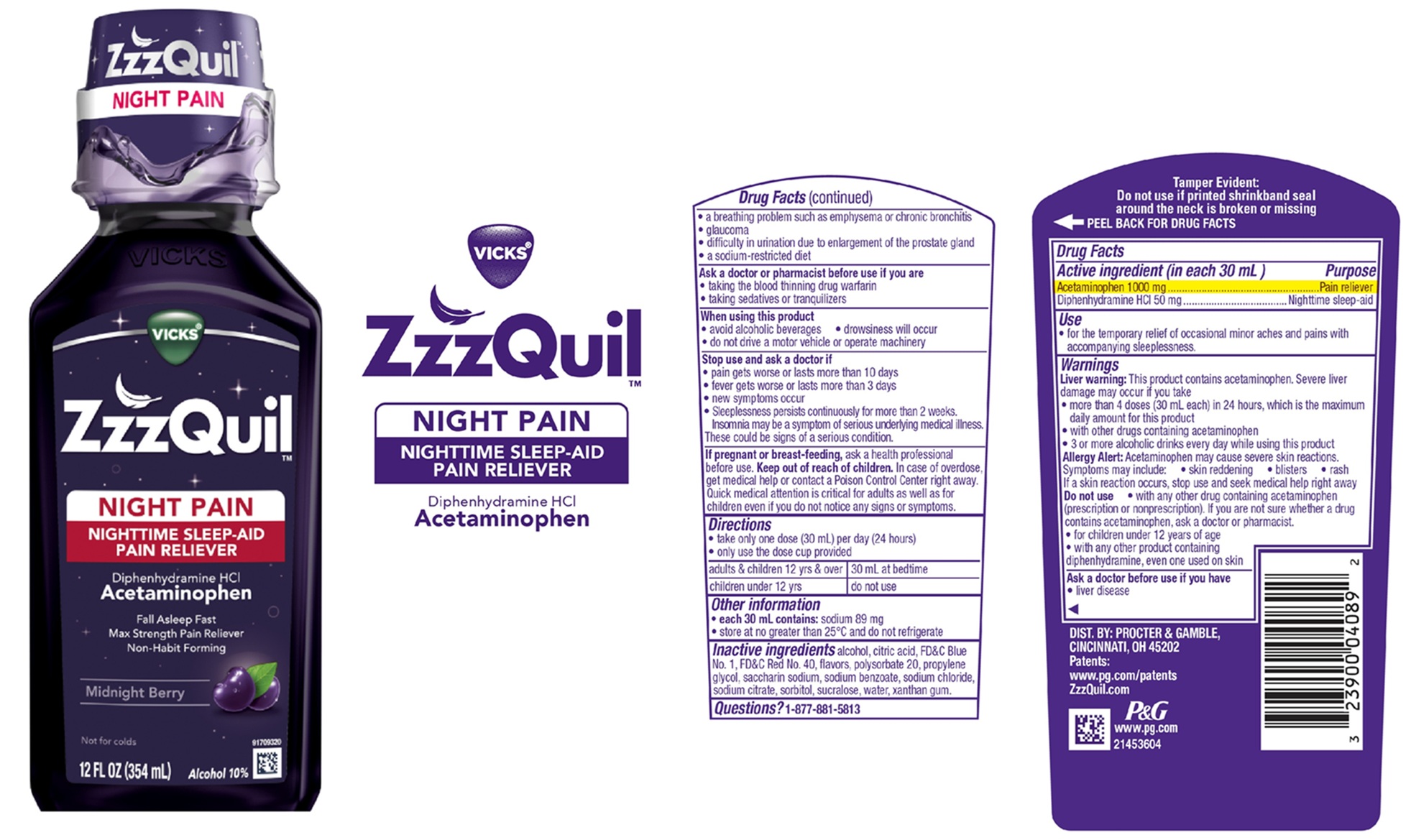 DRUG LABEL: Vicks ZzzQuil
NDC: 37000-598 | Form: LIQUID
Manufacturer: The Procter & Gamble Manufacturing Company
Category: otc | Type: HUMAN OTC DRUG LABEL
Date: 20260220

ACTIVE INGREDIENTS: DIPHENHYDRAMINE HYDROCHLORIDE 50 mg/30 mL; ACETAMINOPHEN 1000 mg/30 mL
INACTIVE INGREDIENTS: ALCOHOL; PROPYLENE GLYCOL; FD&C BLUE NO. 1; CITRIC ACID MONOHYDRATE; POLYSORBATE 20; SACCHARIN SODIUM; WATER; FD&C RED NO. 40; SODIUM BENZOATE; SODIUM CHLORIDE; SODIUM CITRATE; SORBITOL; SUCRALOSE; XANTHAN GUM

VICKS ZzzQuil NIGHT PAIN
NIGHTTIME SLEEP-AID
PAIN RELIEVER

Drug Facts

Active ingredients (in each 30 mL)

Acetaminophen 1000 mg

Diphenhydramine HCl 50 mg

Purpose

Pain reliever

Nighttime sleep-aid

Use

- for the temporary relief of occasional minor aches and pains with accompanying sleeplessness.

Warnings

Liver warning: This product contains acetaminophen. Severe liver damage may occur if you take

• more than 4 doses (30 mL each) in 24 hrs, which is the maximum daily amount for this product

• with other drugs containing acetaminophen

• 3 or more alcoholic drinks every day while using this product

Allergy Alert: Acetaminophen may cause severe skin reactions.

Symptoms may include: • skin reddening • blisters • rash

If a skin reaction occurs, stop use and seek medical help right away

Do not use

• with any other drug containing acetaminophen (prescription or nonprescription). If you are not sure whether a drug contains acetaminophen, ask a doctor or pharmacist.
• for children under 12 years of age
• with any other product containing diphenhydramine, even one used on skin

Ask a doctor before use if you have

- liver disease
- a breathing problem such as emphysema or chronic bronchitis
- glaucoma
- difficulty in urination due to enlargement of the prostate gland
- a sodium-restricted diet

Ask a doctor or pharmacist before use if you are

- taking the blood thinning drug warfarin
- taking sedatives or tranquilizers

When using this product

- avoid alcoholic beverages
- drowsiness will occur
- do not drive a motor vehicle or operate machinery

Stop use and ask a doctor if

- pain gets worse or lasts more than 10 days
- fever gets worse or lasts more than 3 days
- new symptoms occur
- sleeplessness persists continuously for more than 2 weeks. Insomnia may be a symptom of serious underlying medical illness.

These could be signs of a serious condition.

PREGNANCY OR BREAST FEEDING

If pregnant or breast-feeding, ask a health professional before use.

Keep out of reach of children.

OVERDOSAGE

In case of overdose, get medical help or contact a Poison Control Center right away. Quick medical attention is critical for adults as well as for children even if you do not notice any signs or symptoms.

Directions

• take only one dose (30 mL) per day (24 hours)
• only use the dose cup provided

adults & children 12 yrs & over | 30 mL at bedtime
children under 12 yrs | do not use

Other information

- each 30 mL contains: sodium 151 mg
- store at no greater than 25°C and do not refrigerate

Inactive ingredients

alcohol, citric acid, FD&C Blue No. 1, FD&C Red No. 40, flavors, polysorbate 20, propylene glycol, saccharin sodium, sodium benzoate, sodium chloride, sodium citrate, sorbitol, sucralose, water, xanthan gum.

Questions?

1-877-881-5813

Tamper Evident: Do not use if printed shrinkband seal around the neck is broken or missing.

DIST. BY PROCTER & GAMBLE,

CINCINNATI, OH 45202

PRINCIPAL DISPLAY PANEL - 354 ml bottle

VICKS®

ZzzQuil™
NIGHT PAIN
NIGHTTIME SLEEP-AID

PAIN RELIEVER
Diphenhydramine HCl

Acetaminophen

Fall Asleep Fast

Max Strength Pain Reliever

Non-Habit Forming

Midnight Berry

Not for colds

Alcohol 10%

12 FL OZ (354 ml)